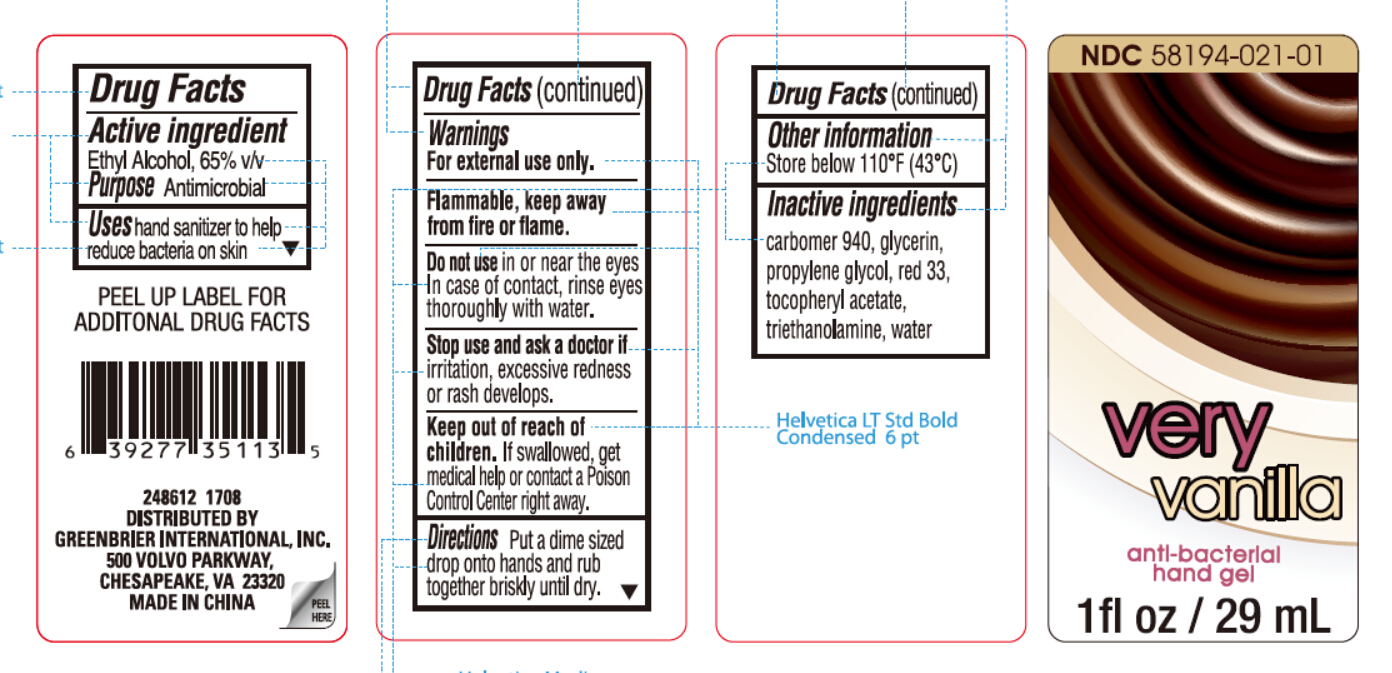 DRUG LABEL: very vanilla
NDC: 71537-004 | Form: GEL
Manufacturer: Huijing (Shanghai) Bio-tech Co., Ltd
Category: otc | Type: HUMAN OTC DRUG LABEL
Date: 20170626

ACTIVE INGREDIENTS: ALCOHOL 65 mL/100 mL
INACTIVE INGREDIENTS: CARBOMER HOMOPOLYMER TYPE C (ALLYL PENTAERYTHRITOL CROSSLINKED); GLYCERIN; PROPYLENE GLYCOL; D&C RED NO. 33; .ALPHA.-TOCOPHEROL ACETATE; TROLAMINE; WATER

Drug Facts

Inactive Ingredients

carbomer 940, glycerin,

propylene glycol, red 33,

tocopheryl acetate,

triethanolamine, water

Active Ingredient

Ethyl Alcohol 65 % v/v

Purpose Antimicrobial

Warnings

For external use only.

Keep out of reach of children. If swallowed,

get medical help or contact a Poison

Control Center right away.

Uses

hand sanitizer to reduce bacteria on skin

DOSAGE AND ADMINISTRATION

Directions Put a dime sized drop onto hands

and rub together briskly until dry.

Do not use in or near the eyes.

In case of contact, rinse eyes

thoroughly with water.

Stop use and ask a doctor

if irritation, excessive redness or

rash develops.

OTHER SAFETY INFORMATION

Flammable. Keep away from

fire or flame.

Other Information

Store below 110° F (43° C)